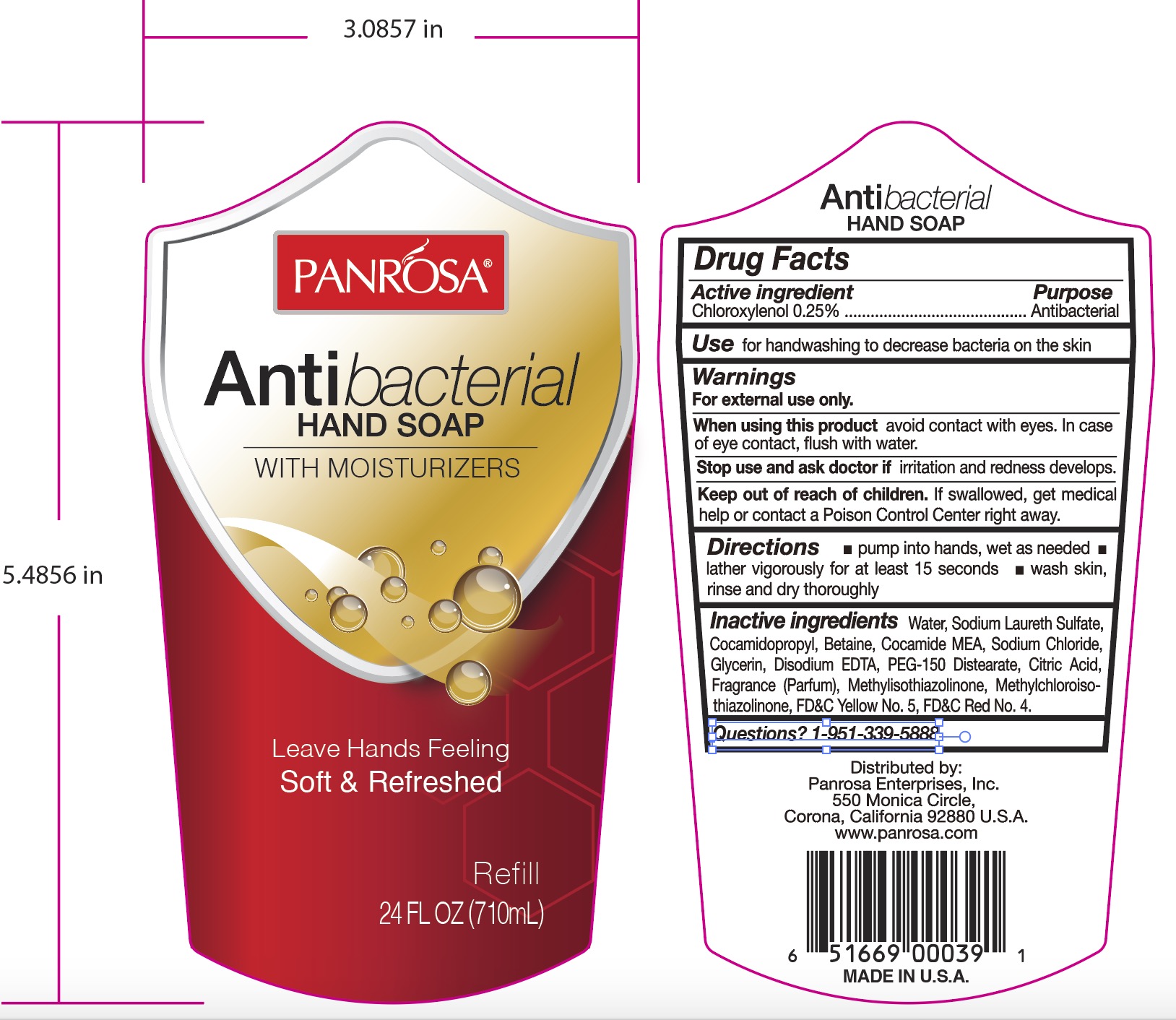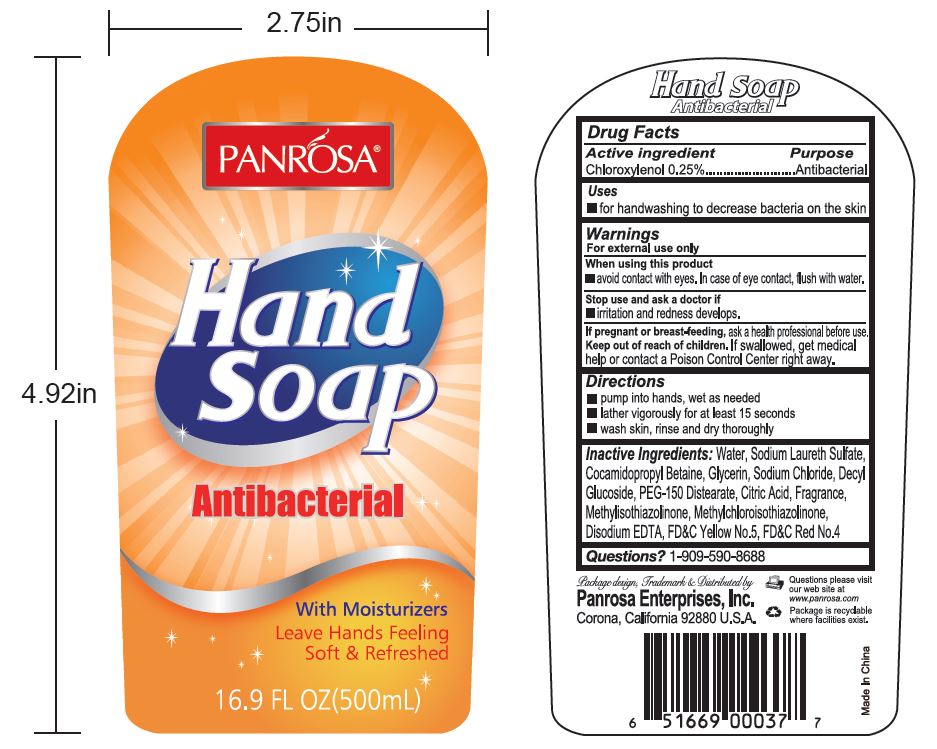 DRUG LABEL: Hand Antibacterial
NDC: 50302-540 | Form: SOAP
Manufacturer: PANROSA ENTERPRISES, INC.
Category: otc | Type: HUMAN OTC DRUG LABEL
Date: 20211020

ACTIVE INGREDIENTS: CHLOROXYLENOL 2.5 mg/1 mL
INACTIVE INGREDIENTS: WATER; SODIUM LAURETH SULFATE; COCO MONOETHANOLAMIDE; COCAMIDOPROPYL BETAINE; GLYCERIN; SODIUM CHLORIDE; EDETATE DISODIUM ANHYDROUS; PEG-150 DISTEARATE; CITRIC ACID MONOHYDRATE; METHYLISOTHIAZOLINONE; METHYLCHLOROISOTHIAZOLINONE; FD&C YELLOW NO. 5; FD&C RED NO. 4

Hand Soap Antibacterial

Active ingredient

Chloroxylenol 0.25%

Purpose

Antibacterial

Uses

- for handwashing to decrease bacteria on the skin

Warnings

For external use only

When using this product

- Avoid contact with eyes. In case of eye contact, flush with water.

Stop use and ask a doctor if

- irritation and redness develops.

Keep out of reach of children.

If swallowed, get medical help or contact a Poison Control Center right away.

Directions

- pump into hands, wet as needed
- lather vigorously for at leat 15 seconds
- wash skin, rinse and dry thoroughly

Inactive Ingredients:

Water, Sodium Laureth Sulfate, Cocamidopropyl Betaine, Cocamide MEA, Sodium Chloride, Glycerin, Disodium EDTA, PEG-150 Distearate, Citric Acid, Fragrance (Parfum), Methylisothiazolinone, Methylchloroisothiazolinone, FD&C Yellow No. 5, FD&C Red No. 4.